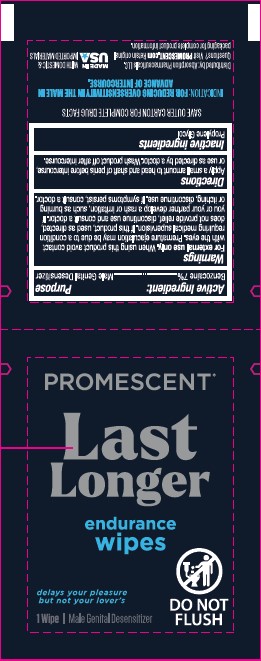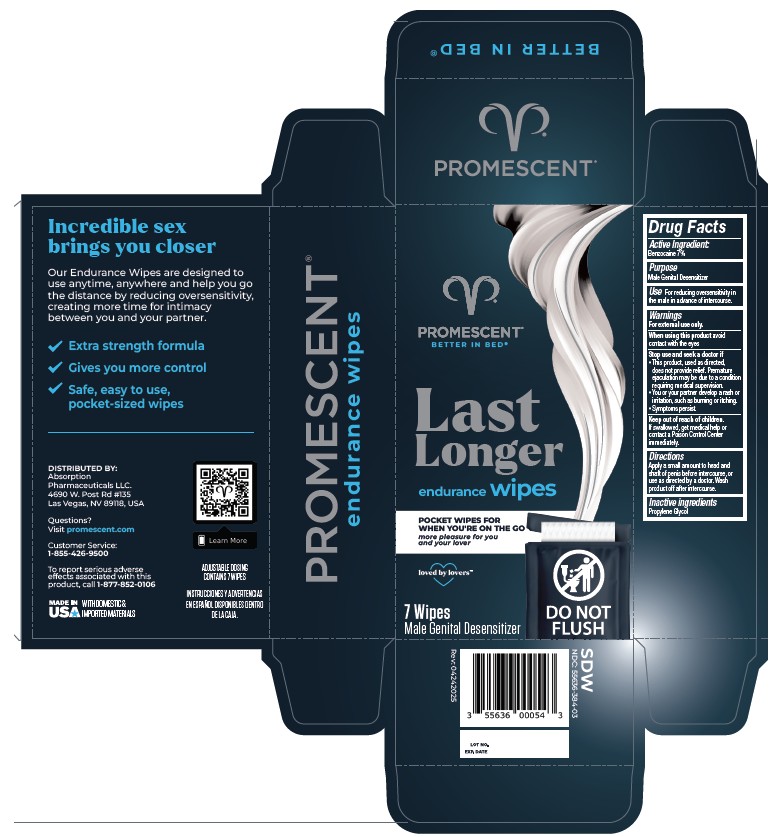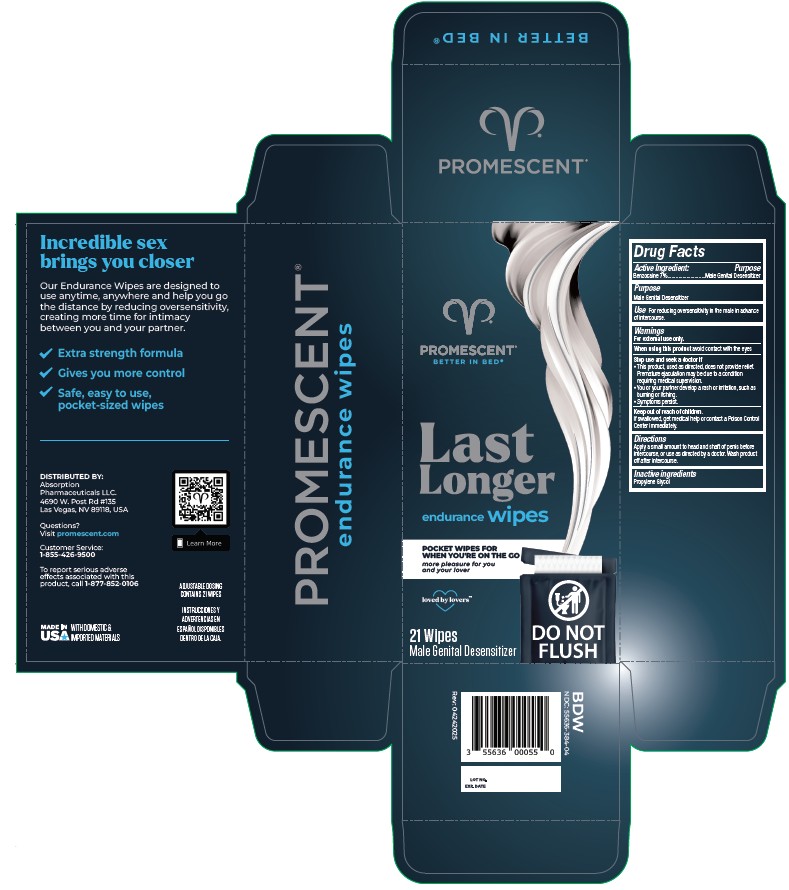 DRUG LABEL: endurance wipe
NDC: 55636-384 | Form: CLOTH
Manufacturer: Absorption Pharmaceuticals, LLC
Category: otc | Type: HUMAN OTC DRUG LABEL
Date: 20260220

ACTIVE INGREDIENTS: BENZOCAINE 7 mg/100 mg
INACTIVE INGREDIENTS: PROPYLENE GLYCOL

PROMESCENT® endurance wipes

Active Ingredient

Benzocaine 7%

Purpose

Male genital desensitizer

Use

For reducing oversensitivity in the male in advance of intercourse.

Warnings

For external use only.

When using this product avoid contact with the eyes

Stop use and seek a doctor if

This product, used as directed, does not provide relief. Premature ejaculation may be due to a condition requiring medical supervision.

You or your partner develop a rash or irritation, such as burning or itching.

Symptoms persist.

Keep out of reach of children. If swallowed, get medical help or contact a Poison Control Center immediately.

Directions

Apply a small amount to head shaft of penis before intercourse, or use as directed by a doctor. Wash product off after intercourse.

Inactive Ingredients

Propylene Glycol

Principal Display Panel

PROMESCENT®

Last Longer

endurance wipes

delays your pleasure

bit not your lover's

1 Wipe | Male Genital Desensitizer

Do Not Flush

SAVE OUTER CARTON FOR COMPLETE DRUG FACTS

INDICATON: FOR REDUCING OVERSENSITIVITY IN IN THE MALE IN

ADVANCE OF INTERCOURSE.

Distributed by: Absorption Pharmaceuticals LLC.

Questions? Visit PROMESCENT.com Retain original

packaging for complete product information.

MADE IN USA WITH DOMESTIC &IMPORTED MATERIALS

PROMESCENT®

BETTER IN BED®

Last Longer

endurance wipes

POCKET WIPES FOR

WHEN YOU'RE ON THE GO

more pleasure for you

and your lover

loved by lovers™

7 Wipes

Male Genital Desensitizer

DO NOT FLUSH

delays your pleasure

bit not your lover's

Incredible sex

brings you closer

Our endurance Wipes are designed to

use anytime, anywhere and help you go

the distance by reducing oversensitivity,

creating more time for intimacy

between you and your partner.

v Extra strength formula

v Gives you more control

v Safe, easy to use, pocket-sized wipes

DISTRIBUTED BY: Absorption Pharmaceuticals LLC.

4690 W. Post Rd #135

Las Vegas, NV 89118, USA

Questions? Visit promescent.com

Customer Service:

1-855-426-9500

To report serious adverse effects associated with this product, call 1-877-852-0106

MADE IN USA WITH DOMESTIC &IMPORTED MATERIALS

ADJUSTABLE DOSING CONTAINS 7 WIPES

INSTRUCCIONESY ADVERTENCIAS EN ESPAÑOL DISPONIBLES DENTRO DE LA CAJA.

7 Wipes

SDW

NDC:55636-384-03

Rev:04242025

21 Wipes

BDW

NDC:55636-384-04

Rev:04242025